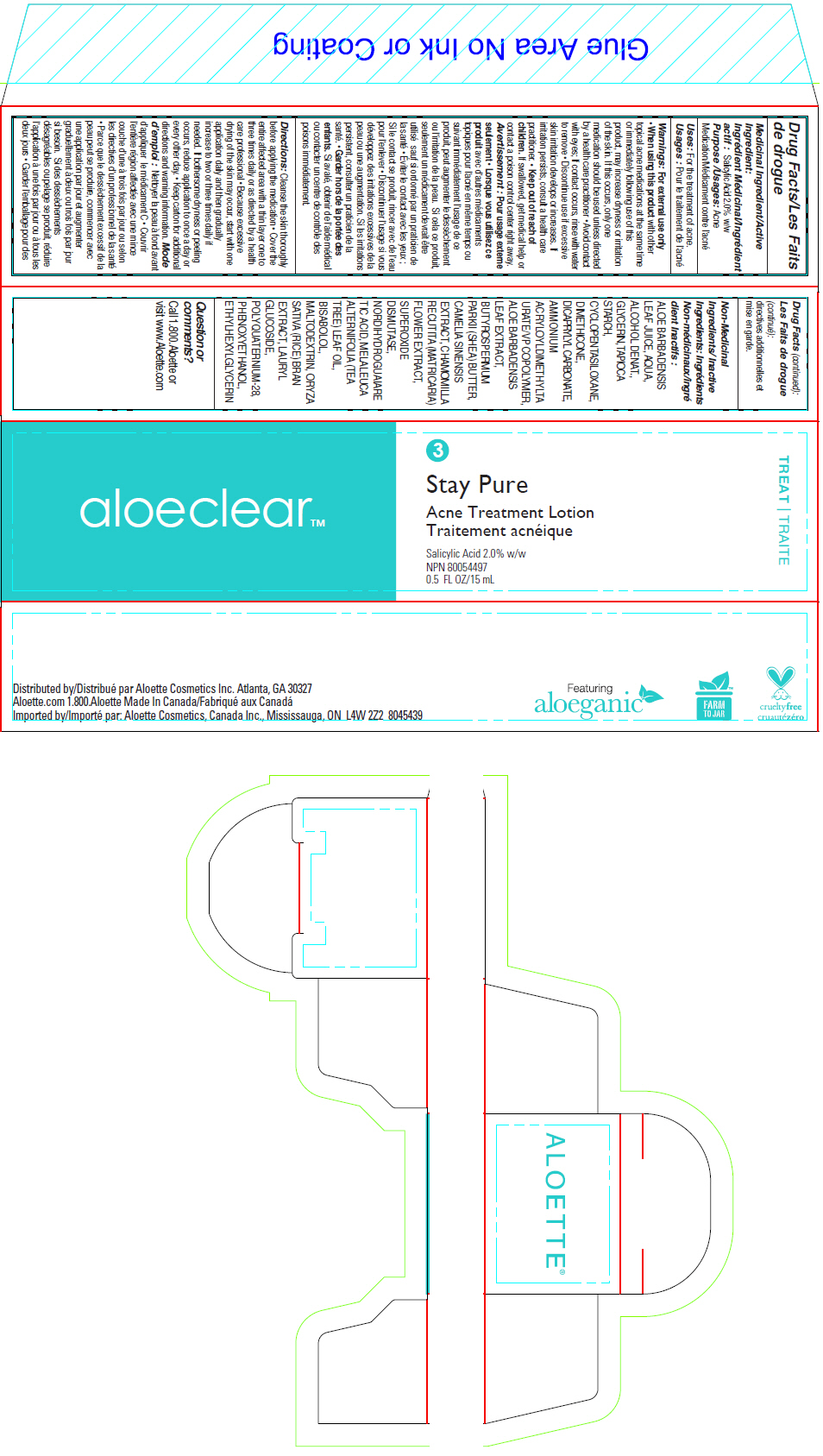 DRUG LABEL: Stay Pure Acne Treatment
NDC: 65447-377 | Form: LOTION
Manufacturer: Aloette
Category: otc | Type: HUMAN OTC DRUG LABEL
Date: 20191227

ACTIVE INGREDIENTS: Salicylic Acid 20 mg/1 mL
INACTIVE INGREDIENTS: ALOE VERA LEAF; WATER; ALCOHOL; GLYCERIN; STARCH, TAPIOCA; CYCLOMETHICONE 5; DIMETHICONE; DICAPRYLYL CARBONATE; SHEA BUTTER; CHAMOMILE; MUSKMELON; MASOPROCOL; TEA TREE OIL; LEVOMENOL; MALTODEXTRIN; RICE BRAN; LAURYL GLUCOSIDE; POLYQUATERNIUM-28 (1100000 MW); PHENOXYETHANOL; ETHYLHEXYLGLYCERIN

Stay Pure Acne Treatment Lotion

Drug Facts

Medicinal Ingredient/Active Ingredient

Salicylic Acid 2.0% w/w

Purpose

Acne Medication

Uses

For the treatment of acne.

Warnings

For external use only

- When using this product with other topical acne medications at the same time or immediately following use of this product, may increase dryness or irritation of the skin. If this occurs, only one medication should be used unless directed by a health care practitioner
- Avoid contact with eyes; If contact occurs, rinse with water to remove

STOP USE

- Discontinue use if excessive skin irritation develops or increases. If irritation persists, consult a health care practitioner.

- Keep out of reach of children. If swallowed, get medical help or contact a poison control center right away.

Directions

Cleanse the skin thoroughly before applying the medication

- Cover the entire affected area with a thin layer one to three times daily or as directed by a health care professional
- Because excessive drying of the skin may occur, start with one application daily and then gradually increase to two or three times daily if needed. If bothersome dryness or peeling occurs, reduce application to once a day or every other day.
- Keep carton for additional directions and warning information.

Non-Medicinal Ingredients/Inactive Ingredients

ALOE BARBADENSIS LEAF JUICE, AQUA, ALCOHOL DENAT., GLYCERIN, TAPIOCA STARCH, CYCLOPENTASILOXANE, DIMETHICONE, DICAPRYLYL CARBONATE, AMMONIUM ACRYLOYLDIMETHYLTA URATE/VP COPOLYMER, ALOE BARBADENSIS LEAF EXTRACT, BUTYROSPERMUM PARKII (SHEA) BUTTER, CAMELIA SINENSIS EXTRACT, CHAMOMILLA RECUTITA (MATRICARIA) FLOWER EXTRACT, SUPEROXIDE DISMUTASE, NORDIHYDROGUAIARE TIC ACID, MELALEUCA ALTERNIFOLIA (TEA TREE) LEAF OIL, BISABOLOL, MALTODEXTRIN, ORYZA SATIVA (RICE) BRAN EXTRACT, LAURYL GLUCOSIDE, POLYQUATERNIUM-28, PHENOXYETHANOL, ETHYLHEXYLGLYCERIN

Question or comments?

Call 1.800.Aloette or visit www.Aloette.com

Distributed by Aloette Cosmetics Inc. Atlanta, GA 30327

PRINCIPAL DISPLAY PANEL - 15 mL Tube Carton

aloeclear™

3

Stay Pure

Acne Treatment Lotion

Salicylic Acid 2.0% w/w
NPN 80054497
0.5 FL OZ/15 mL

TREAT